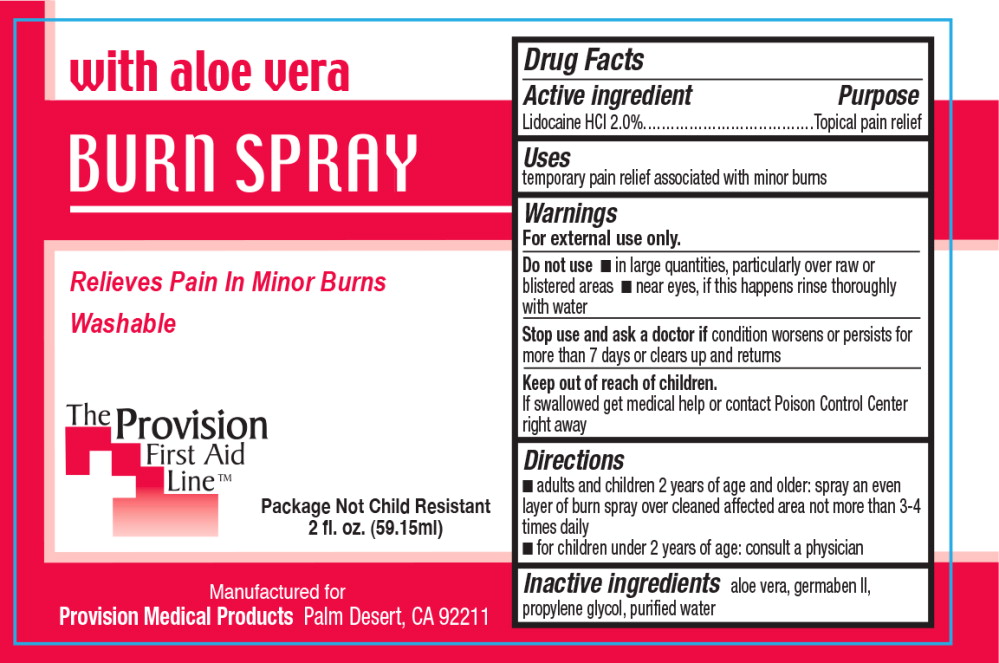 DRUG LABEL: Burn with Aloe
NDC: 69103-3500 | Form: SPRAY
Manufacturer: Provision Medical
Category: otc | Type: HUMAN OTC DRUG LABEL
Date: 20140724

ACTIVE INGREDIENTS: Lidocaine Hydrochloride 200 g/1 L
INACTIVE INGREDIENTS: aloe vera leaf; propylene glycol; propylparaben; methylparaben; diazolidinyl urea; water

Drug Facts

Active ingredient

Lidocaine HCI 2,0%

Purpose

Topical pain relief

Uses

temporary pain relief associated with minor burns

Warnings

For external use only.

Do not use

- in large quantities, particularly over raw or blistered areas
- near eyes, if this happens rinse thoroughly with water

Stop use and ask a doctor if condition worsens or persists for more than 7 days or clears up and returns

Keep out of reach of children.

If swallowed get medical help or contact Poison Control Center right away

Directions

- adults and children 2 years of age and older: spray an even layer of burn spray over cleaned affected area not more than 3-4 times daily
- for children under 2 years of age: consult a physician

Inactive ingredients

aloe vera, germaben II, propylene glycol, purified water

Principal Display Panel - Bottle Label

with aloe vera

BURN SPRAY

Relieves Pain in Minor Burns

Washable

Package Not Child Resistant

2 fl. oz. (59.15ml)

Manufactured for

Provision Medical Products Palm Desert, CA 92211